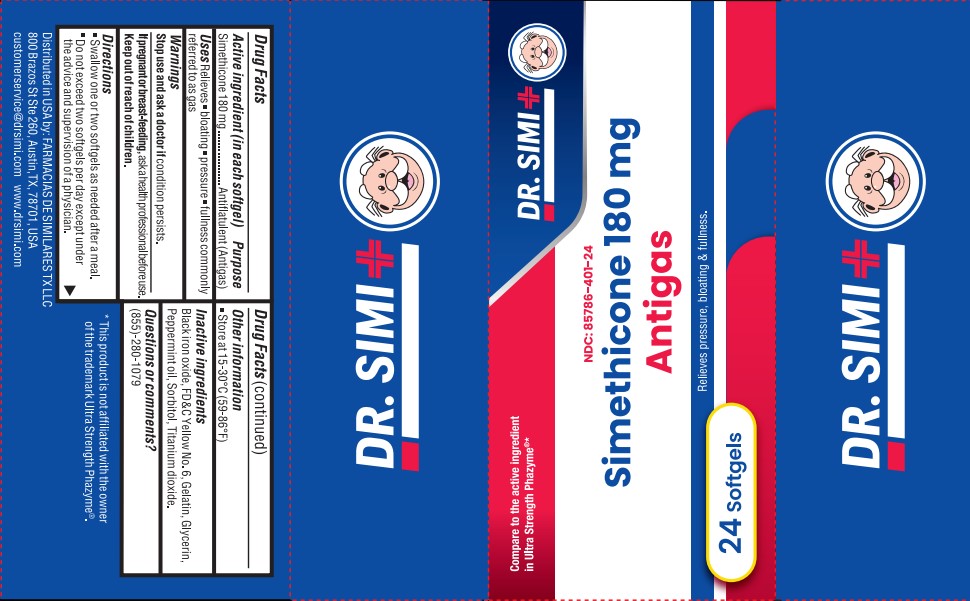 DRUG LABEL: Simethicone 180 MG
NDC: 85786-401 | Form: CAPSULE, LIQUID FILLED
Manufacturer: Farmacias De Similares TX LLC
Category: otc | Type: HUMAN OTC DRUG LABEL
Date: 20260101

ACTIVE INGREDIENTS: DIMETHICONE 180 mg/1 1
INACTIVE INGREDIENTS: TITANIUM DIOXIDE; FD&C YELLOW NO. 6; GELATIN; PEPPERMINT OIL; GLYCERIN; FERROSOFERRIC OXIDE; SORBITOL

Active ingredient (in each softgel)

Simethicone 180 mg

Purpose

Antiflatulent (antigas)

Uses

Relieves - bloating - pressure -fullness commonly referred to as gas

Warnings

Stop use and ask a doctor if

condition persists.

If pregnant or breast-feeding,

ask a health professional before use.

Keep out of reach of children.

Directions

- Swallow one or two softgels as needed after a meal.
- Do not exceed two softgels per day except under the advice and supervision of a physician.

Other information

Store at 15-30°C (59-86°F)

Inactive ingredients

Black iron oxide, FD&C Yellow No. 6, Gelatin, Glycerin, Peppermint oil, Sorbitol, Titanium dioxide.

Questions or comments?

(855)-280-1079

* This product is not affiliated with the owner of the trademark Ultra Strength Phazyme®.

Distributed in USA by: FARMACIAS DE SIMILARES TX LLC
800 Brazos St Ste 260, Austin, TX, 78701, USA
customerservice@drsimi.com www.drsimi.com

PACKAGE LABEL

Dr. Simi

Compare to the active ingredient in Ultra Strength Phazyme®*

NDC: 85786-401-24

Simethicone 180 mg

Antigas

Relieves pressure, bloating & fullness.

24 Softgels